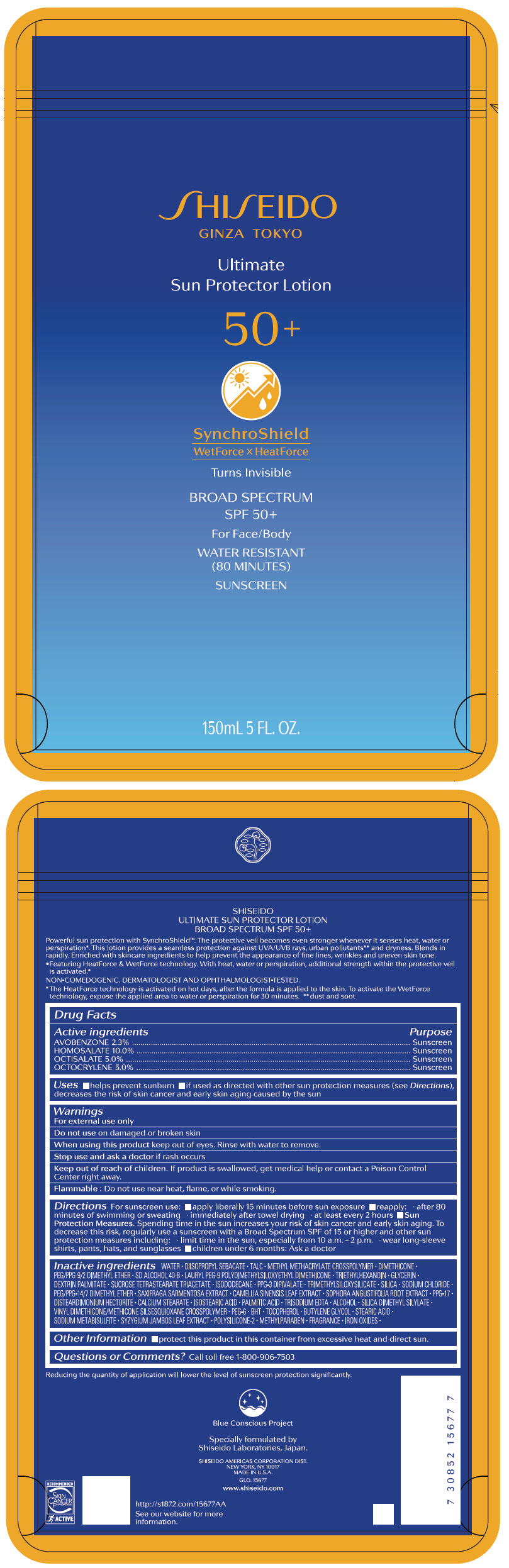 DRUG LABEL: SHISEIDO ULTIMATE SUN PROTECTOR
NDC: 58411-481 | Form: LOTION
Manufacturer: SHISEIDO AMERICAS CORPORATION
Category: otc | Type: HUMAN OTC DRUG LABEL
Date: 20250320

ACTIVE INGREDIENTS: OCTISALATE 50 mg/1 mL; HOMOSALATE 100 mg/1 mL; OCTOCRYLENE 50 mg/1 mL; AVOBENZONE 23 mg/1 mL
INACTIVE INGREDIENTS: WATER; DIISOPROPYL SEBACATE; TALC; METHYL METHACRYLATE/GLYCOL DIMETHACRYLATE CROSSPOLYMER; DIMETHICONE; PEG/PPG-9/2 DIMETHYL ETHER; LAURYL PEG-9 POLYDIMETHYLSILOXYETHYL DIMETHICONE; TRIETHYLHEXANOIN; GLYCERIN; DEXTRIN PALMITATE (CORN; 20000 MW); SUCROSE TETRASTEARATE TRIACETATE; ISODODECANE; TRIMETHYLSILOXYSILICATE (M/Q 0.6-0.8); SILICON DIOXIDE; SODIUM CHLORIDE; PEG/PPG-14/7 DIMETHYL ETHER; SAXIFRAGA STOLONIFERA LEAF; GREEN TEA LEAF; SOPHORA FLAVESCENS ROOT; PPG-17; DISTEARDIMONIUM HECTORITE; CALCIUM STEARATE; ISOSTEARIC ACID; PALMITIC ACID; EDETATE TRISODIUM; ALCOHOL; SILICA DIMETHYL SILYLATE; VINYL DIMETHICONE/METHICONE SILSESQUIOXANE CROSSPOLYMER; POLYETHYLENE GLYCOL 300; BUTYLATED HYDROXYTOLUENE; .ALPHA.-TOCOPHEROL; BUTYLENE GLYCOL; STEARIC ACID; SODIUM METABISULFITE; SYZYGIUM JAMBOS LEAF; METHYLPARABEN; FERRIC OXIDE RED; FERRIC OXIDE YELLOW; FERROSOFERRIC OXIDE

SHISEIDO ULTIMATE SUN PROTECTOR LOTION

Drug Facts

ACTIVE INGREDIENT

Active ingredients | Purpose
Octisalate 5.0% | Sunscreen
Avobenzone 2.3% | Sunscreen
Homosalate 10.0% | Sunscreen
Octocrylene 5.0% | Sunscreen

Uses

- helps prevent sunburn
- if used as directed with other sun protection measures (see Directions), decreases the risk of skin cancer and early skin aging caused by the sun

Warnings

For external use only

Do not use on damaged or broken skin

When using this product keep out of eyes. Rinse with water to remove.

Stop use and ask a doctor if rash occurs.

Keep out of reach of children. If product is swallowed, get medical help or contact a Poison Control Center right away.

Flammable: Do not use near heat, flame, or while smoking.

Directions

For sunscreen use:

- apply liberally 15 minutes before sun exposure
- reapply:
  - after 80 minutes of swimming or sweating
  - immediately after towel drying
  - at least every two hours
- Sun Protection Measures. Spending time in the sun increases your risk of skin cancer and early skin aging. To decrease this risk, regularly use a sunscreen with a broad spectrum SPF of 15 or higher and other sun protection measures including:
  - limit time in the sun, especially from 10 a.m. – 2 p.m.
  - wear long-sleeve shirts, pants, hats, and sunglasses
  - children under 6 months: Ask a doctor

Inactive Ingredients

:WATER▪DIISOPROPYL SEBACATE▪TALC▪METHYL METHACRYLATE CROSSPOLYMER▪DIMETHICONE▪PEG/PPG-9/2 DIMETHYL ETHER▪SD ALCOHOL 40-B▪LAURYL PEG-9 POLYDIMETHYLSILOXYETHYL DIMETHICONE▪TRIETHYLHEXANOIN▪GLYCERIN▪DEXTRIN PALMITATE▪SUCROSE TETRASTEARATE TRIACETATE▪ISODODECANE▪PPG-3 DIPIVALATE▪TRIMETHYLSILOXYSILICATE▪SILICA▪SODIUM CHLORIDE▪PEG/PPG-14/7 DIMETHYL ETHER▪SAXIFRAGA SARMENTOSA EXTRACT▪CAMELLIA SINENSIS LEAF EXTRACT▪SOPHORA ANGUSTIFOLIA ROOT EXTRACT▪PPG-17▪DISTEARDIMONIUM HECTORITE▪CALCIUM STEARATE▪ISOSTEARIC ACID▪PALMITIC ACID▪TRISODIUM EDTA▪ALCOHOL▪SILICA DIMETHYL SILYLATE▪VINYL DIMETHICONE/METHICONE SILSESQUIOXANE CROSSPOLYMER▪PEG-6▪BHT▪TOCOPHEROL▪BUTYLENE GLYCOL▪STEARIC ACID▪SODIUM METABISULFITE▪SYZYGIUM JAMBOS LEAF EXTRACT▪POLYSILICONE-2▪METHYLPARABEN▪FRAGRANCE▪IRON OXIDES▪

Other information

Protect this product in this container from excessive heat and direct sun.

Questions or comments?

Call toll free 1-800-906-7503

PRINCIPAL DISPLAY PANEL - 150 mL Bottle Label

SHISEIDO
GINZA TOKYO

Ultimate
Sun Protector Lotion

50+

SynchroShield
WetForce x HeatForce

Turns Invisible

BROAD SPECTRUM
SPF 50+

For Face/Body

WATER RESISTANT
(80 MINUTES)

SUNSCREEN

150mL 5 FL. OZ.